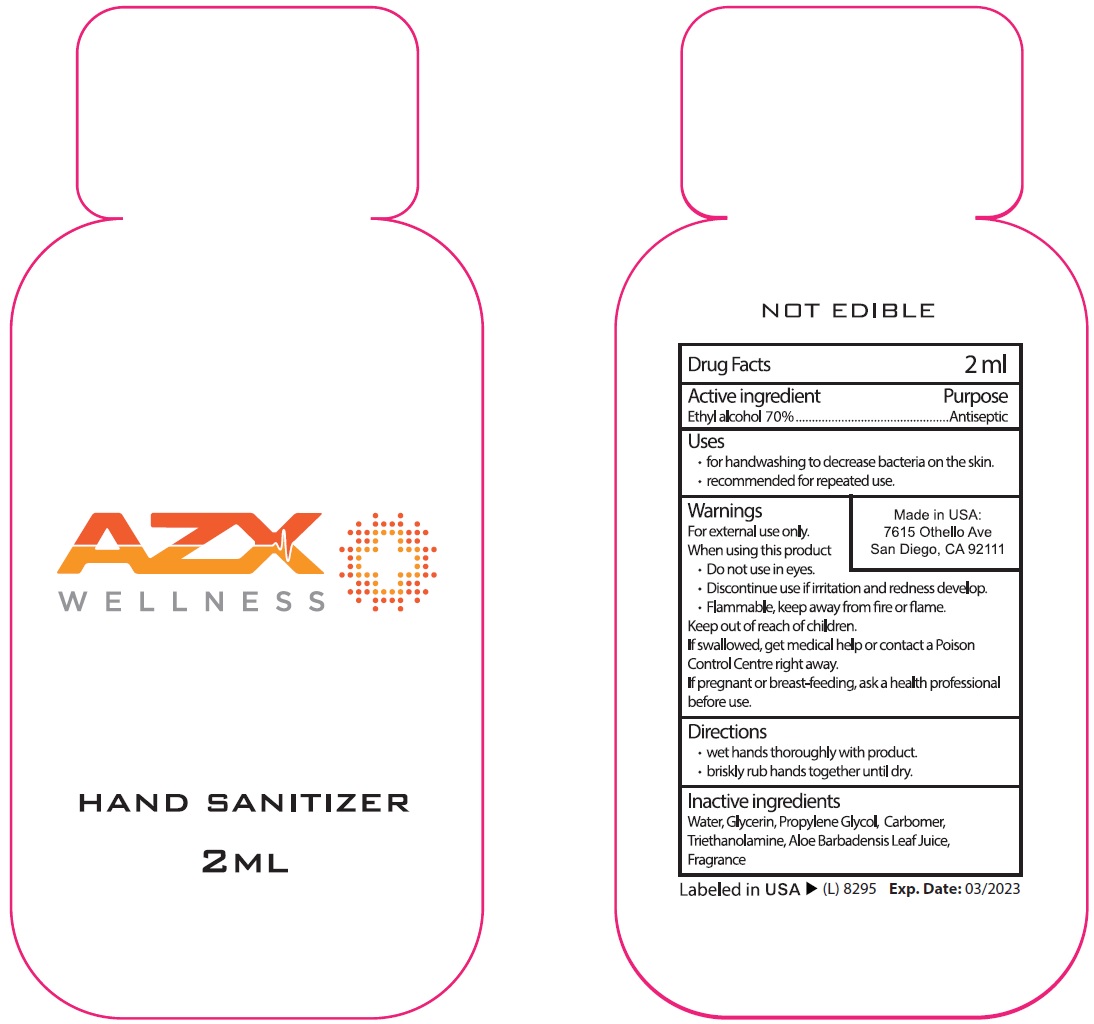 DRUG LABEL: AZX Wellness Hand Sanitizer
NDC: 73145-012 | Form: GEL
Manufacturer: ASC Marketing LTD
Category: otc | Type: HUMAN OTC DRUG LABEL
Date: 20231201

ACTIVE INGREDIENTS: ALCOHOL 70 mL/100 mL
INACTIVE INGREDIENTS: WATER; GLYCERIN; PROPYLENE GLYCOL; CARBOMER HOMOPOLYMER, UNSPECIFIED TYPE; TROLAMINE; ALOE VERA LEAF

AZX Wellness Hand Sanitizer

Active ingredient

Ethyl alcohol 70%

Purpose

Antiseptic

Uses

- for handwashing to decrease bacteria on the skin.
- recommended for repeated use.

Warnings

For external use only.

When using this product

- Do not use in eyes.
- Discontinue use if irritation and redness develop.
- Flammable, keep away from fire or flame.

Keep out of reach of children.

If swallowed, get medical help or contact a Poison Control Centre right away.

If pregnant or breast-feeding,

ask a health professional before use.

Directions

• wet hands thoroughly with product. • briskly rub hands together until dry.

Inactive ingredients

Water, Glycerin, Propylene Glycol, Carbomer, Triethanolamine, Aloe Barbadensis Leaf Juice, Fragrance